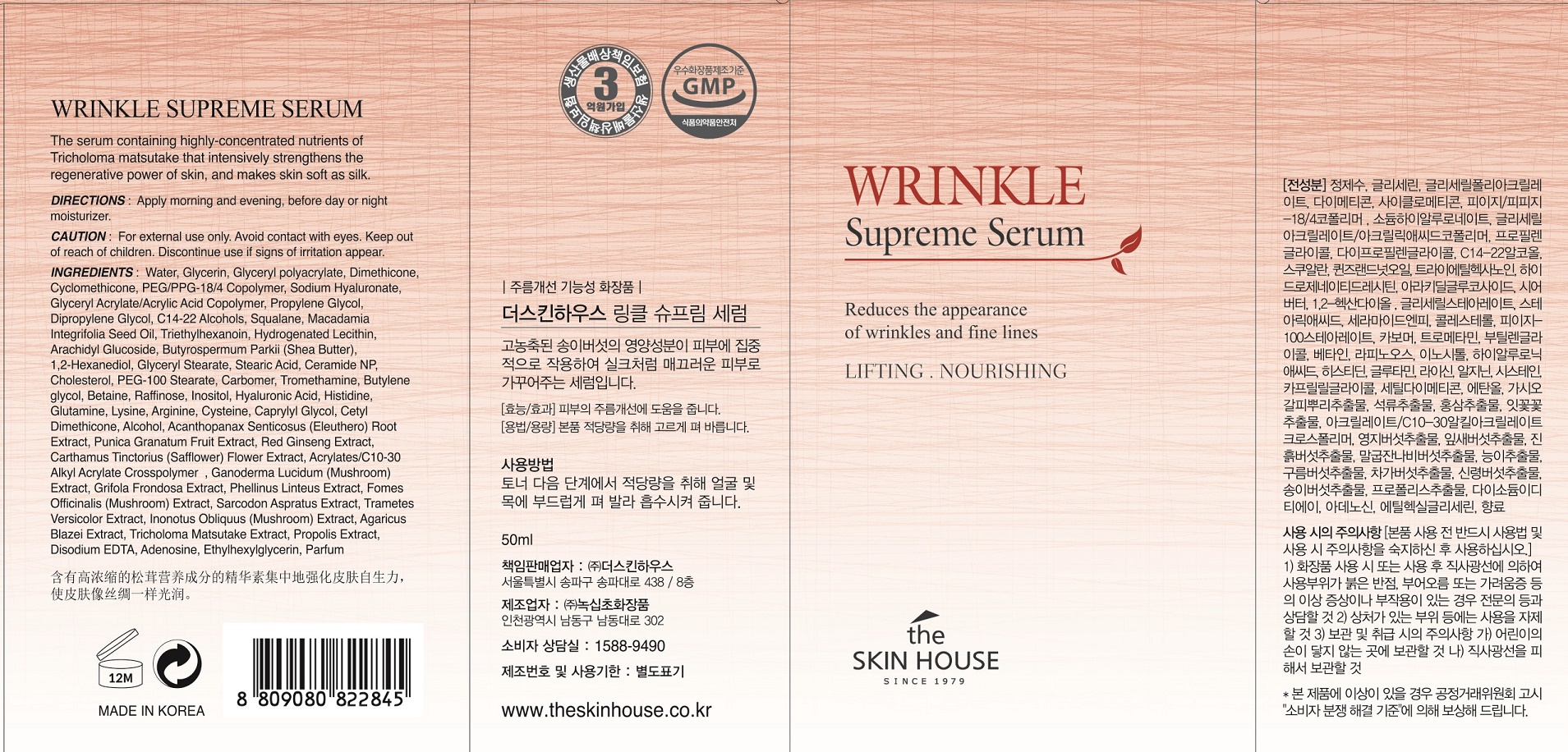 DRUG LABEL: THE SKINHOUSE WRINKLE SUPREME SERUM
NDC: 73590-0007 | Form: LIQUID
Manufacturer: NOKSIBCHO cosmetic Co., Ltd.
Category: otc | Type: HUMAN OTC DRUG LABEL
Date: 20200129

ACTIVE INGREDIENTS: ASIAN GINSENG 0.5 g/100 mL
INACTIVE INGREDIENTS: WATER; BUTYLENE GLYCOL

Drug Facts

ACTIVE INGREDIENT

Panax Ginseng Root Extract, Ganoderma Lucidum (Mushroom) Extract, Phellinus Linteus Extract, Inonotus Obliquus (Mushroom) Extract, Agaricus Blazei Extract, Tricholoma Matsutake Extract, Hizikia Fusiforme Extract, Codium Tomentosum Extract, Gelidium Cartilagineum Extract.

INACTIVE INGREDIENT

Water
Glycerin
Glyceryl polyacrylate
Dimethicone
Cyclomethicone
PEG/PPG-18/4 Copolymer
Sodium Hyaluronate
Glycerin
Glyceryl Acrylate/Acrylic Acid Copolymer
Propylene Glycol
Dipropylene Glycol
Dimethicone
Water
Glycerin
C14-22 Alcohols
Squalane
Macadamia Integrifolia Seed Oil
Triethylhexanoin
Hydrogenated Lecithin
Arachidyl Glucoside
Butyrospermum Parkii (Shea Butter)
1,2-Hexanediol
Glyceryl Stearate
Stearic Acid
Ceramide NP
Cholesterol
PEG-100 Stearate
Dimethicone
Carbomer
Tromethamine
Water
Butylene glycol
Betaine
Raffinose
Inositol
Hyaluronic Acid
Histidine
Glutamine
Glycerin
Lysine
Arginine
Cysteine
1,2-Hexanediol
Caprylyl Glycol
1,2-Hexanediol
Cetyl Dimethicone
Butylene glycol
Ceramide NP
Hydrogenated Lecithin
Glycerin
Propylene Glycol
Alcohol
Water
Acanthopanax Senticosus (Eleuthero) Root Extract
Punica Granatum Fruit Extract
Red Ginseng Extract
Carthamus Tinctorius (Safflower) Flower Extract
Red Ginseng Extract
Arginine
Acrylates/C10-30 Alkyl Acrylate Crosspolymer
Ganoderma Lucidum (Mushroom) Extract
Grifola Frondosa Extract
Phellinus Linteus Extract
Fomes Officinalis (Mushroom) Extract
Sarcodon Aspratus Extract
Trametes Versicolor Extract
Inonotus Obliquus (Mushroom) Extract
Agaricus Blazei Extract
Tricholoma Matsutake Extract
Propolis Extract
Disodium EDTA
Adenosine
Ethylhexylglycerin
Parfum

PURPOSE

- Anti-wrinkle function serum

The sticky transparent essence contains ginseng extract and high-enriched 9 types of mushroom’s nutrition and it makes skin elastic and smooth. It fills up skin with basic nutrition and the adenosine which is the wrinkle improvement ingredient will help improving micro wrinkles to become elastic and smooth skin. Also, imakes skin healthy and shiny by relieving stress of tired skin from stress and fine dust and providing vitality to skin. Especially, the antioxidant ingredients from mushroom will help the skin to become baby face.

keep out of reach of the children

INDICATIONS AND USAGE

After cleansing, use toner to smooth the skin texture.
Apply enough serum to the face, and let it be absorbed deeply into skin.

* It gives you the synergy effect, when used before the emulsion

WARNINGS

For external use only
When using this product

■ if the following symptoms occurs after use, stop use and consult with a skin specialist

red specks, swelling, itching

■ don’t use on the part where there is injury, eczema, or dermatitis

Keep out of reach of children

■ if swallowed, get medical help or contact a person control center immediately

DOSAGE AND ADMINISTRATION

for external use only